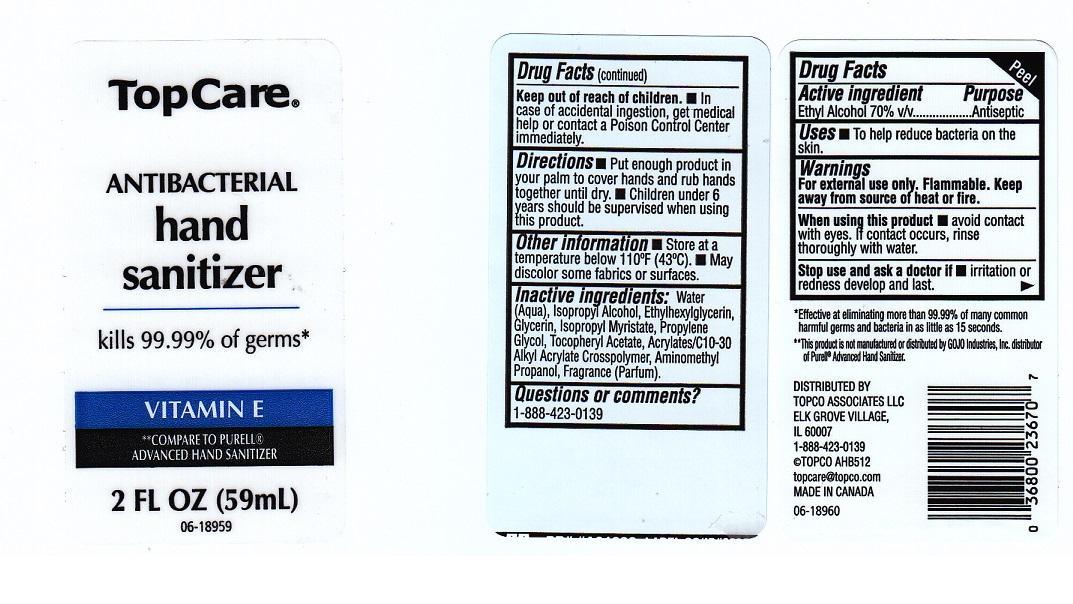 DRUG LABEL: TOPCARE
NDC: 36800-078 | Form: LIQUID
Manufacturer: TOPCO ASSOCIATES LLC
Category: otc | Type: HUMAN OTC DRUG LABEL
Date: 20131227

ACTIVE INGREDIENTS: ALCOHOL 700 mg/1 mL
INACTIVE INGREDIENTS: WATER; ISOPROPYL ALCOHOL; ETHYLHEXYLGLYCERIN; GLYCERIN; ISOPROPYL MYRISTATE; PROPYLENE GLYCOL; .ALPHA.-TOCOPHEROL ACETATE; CARBOMER COPOLYMER TYPE A (ALLYL PENTAERYTHRITOL CROSSLINKED); AMINOMETHYLPROPANOL

DRUG FACTS

ACTIVE INGREDIENT

ETHYL ALCOHOL 70% V/V

PURPOSE

ANTISEPTIC

USES

TO HELP REDUCE BACTERIA ON THE SKIN

WARNINGS

FOR EXTERNAL USE ONLY. FLAMMABLE. KEEP AWAY FROM SOURCE OF HEAT OR FIRE

WHEN USING THIS PRODUCT

AVOID CONTACT WITH EYES. IF CONTACT OCCURS, RINSE THOROUGHLY WITH WATER

STOP USE AND ASK A DOCTOR IF

IRRITATION OR REDNESS DEVELOP AND LAST

KEEP OUT OF REACH OF CHILDREN

IN CASE OF ACCIDENTAL INGESTION, GET MEDICAL HELP OR CONTACT A POISON CONTROL CENTER IMMEDIATELY

DIRECTIONS

PUT ENOUGH PRODUCT IN YOUR PALM TO COVER HANDS AND RUB HANDS TOGETHER UNTIL DRY. CHILDREN UNDER 6 YEARS SHOULD BE SUPERVISED WHEN USING THIS PRODUCT

OTHER INFORMATION

STORE AT A TEMPERATURE BELOW 110°F (43°C). MAY DISCOLOR SOME FABRICS OR SURFACES

INACTIVE INGREDIENTS

WATER (AQUA), ISOPROPYL ALCOHOL, ETHYLHEXYLGLYCERIN, GLYCERIN, ISOPROPYL MYRISTATE, PROPYLENE GLYCOL, TOCOPHERYL ACETATE, ACRYLATES/C10-30 ALKYL ACRYLATE CROSSPOLYMER, AMINOMETHYL PROPANOL, FRAGRANCE (PARFUM)

QUESTIONS OR COMMENTS?

1-888-423-0139